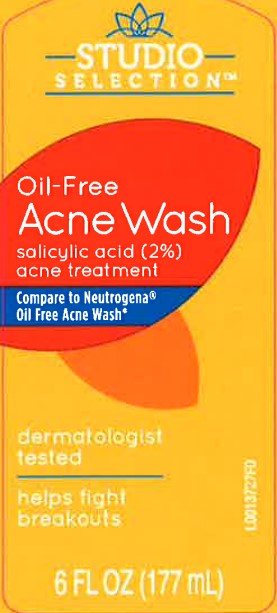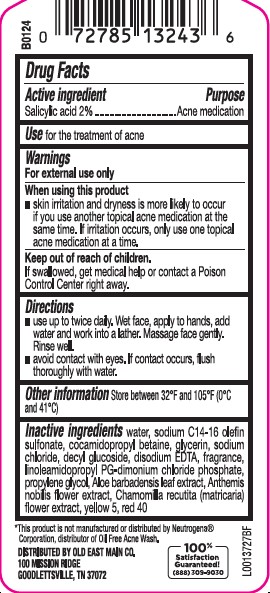 DRUG LABEL: Acne Wash
NDC: 55910-947 | Form: LOTION
Manufacturer: Old East Main Co.
Category: otc | Type: HUMAN OTC DRUG LABEL
Date: 20260302

ACTIVE INGREDIENTS: SALICYLIC ACID 20 mg/1 mL
INACTIVE INGREDIENTS: WATER; SODIUM C14-16 OLEFIN SULFONATE; COCAMIDOPROPYL BETAINE; GLYCERIN; SODIUM CHLORIDE; DECYL GLUCOSIDE; EDETATE DISODIUM ANHYDROUS; LINOLEAMIDOPROPYL PG-DIMONIUM CHLORIDE PHOSPHATE; PROPYLENE GLYCOL; ALOE VERA LEAF; CHAMAEMELUM NOBILE FLOWER; CHAMOMILE; FD&C YELLOW NO. 5; FD&C RED NO. 40

Studio Selection 947.003/947AC-AD
Oil Free Acne Wash

Active ingredient

Salicylic acid 2%

Purpose

Acne medication

Use

For the treatment of acne

Warnings

For external use only

When using this product

- skin irritation and dryness is more likely to occur if you use another topical acne medication at the same time. If irritation occurs, only use one topical acne medication at a time

Keep out of reach of children

If swallowed, get medical help or contact a Poison Control Center right away.

Directions

- use up to twice a day. Wet face, apply to hands, add water and work into lather. Massage face gently. Rinse well.
- avoid contact with eyes. If contact occurs, flush thoroughly with water.

Inactive ingredients

water, sodium C14-16 olefin sulfonate, cocamidopropyl betaine, glycerin, sodium chloride, decyl glucoside, disodium EDTA, fragrance, linoleamidopropyl PG-dimonium chloride phosphate, propylene glycol, Aloe barbadensis leaf extract, Anthemis nobilis flower extract, Chamomilla recutita (matricaria) flower extract, yellow 5, red 40

Disclaimer

*This product is not manufactured or distributed by Neutrogena®Corporation, distributor of Oil-Free Acne Wash.

Adverse Reaction

DISTRIBUTED BY OLD EAST MAIN CO.

100 Mission Ridge,

Goodlettsville, TN 37072

100% Satisfaction Guaranteed!

(888) 309-9030

Principal display panel

STUDIO SELECTION™

Oil-Free

Acne Wash

Salicylic Acid 2%

acne Treatment

Compare to Neutrogena®Oil-Free Acne Wash*

dermatologist tested

helps fight breakouts

6 FL OZ (177 mL)